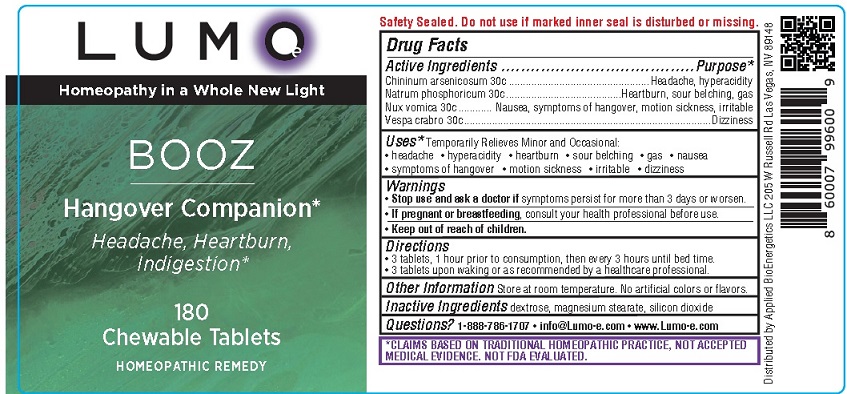 DRUG LABEL: LUMO Booz Hangover Companiion
NDC: 81425-003 | Form: TABLET, CHEWABLE
Manufacturer: Applied Bioenergetics, LLC
Category: homeopathic | Type: HUMAN OTC DRUG LABEL
Date: 20251110

ACTIVE INGREDIENTS: QUININE ARSENITE 30 [hp_C]/1 1; SODIUM PHOSPHATE, DIBASIC, HEPTAHYDRATE 30 [hp_C]/1 1; STRYCHNOS NUX-VOMICA SEED 30 [hp_C]/1 1; VESPA CRABRO 30 [hp_C]/1 1
INACTIVE INGREDIENTS: DEXTROSE; MAGNESIUM STEARATE; SILICON DIOXIDE

LUMO-e Booz Hangover Companiion

Drug Facts

Active Ingredients
Chininum arsenicosum ......30c
Natrum phosphoricum .......30c
Nux vomica ......................30c
Vespa crabro ....................30c

Purpose*
Chininum arsenicosum .................................................Headache, hyperacidity
Natrum phosphoricum .........................................Heartburn, sour belching, gas
Nux vomica ............ Nausea, symptoms of hangover, motion sickness, irritable
Vespa crabro ..................................................................................Dizziness

INDICATIONS AND USAGE

Uses* Temporarily Relieves Minor and Occasional:
• headache • hyperacidity • heartburn • sour belching • gas • nausea
• symptoms of hangover • motion sickness • irritable • dizziness

Warnings
• Stop use and ask a doctor if symptoms persist for more than 3 days or worsen.
• If pregnant or breastfeeding, consult your health professional before use.

• Keep out of reach of children.

Directions
• 3 tablets, 1 hour prior to consumption, then every 3 hours until bed time.
• 3 tablets upon waking or as recommended by a healthcare professional.

Other Information Store at room temperature. No artificial colors or flavors.

Inactive Ingredients dextrose, magnesium stearate, silicon dioxide

QUESTIONS

Questions? 1-888-786-1707 • info@Lumo-e.com • www.Lumo-e.com

*CLAIMS BASED ON TRADITIONAL HOMEOPATHIC PRACTICE, NOT ACCEPTED
MEDICAL EVIDENCE. NOT FDA EVALUATED.

Product Label for LUMO-e BOOZ

LUMO-e
Homeopathy in a Whole New Light

BOOZ

Hangover Companion*
Headache, Heartburn,
Indigestion*

180
Chewable Tablets

HOMEOPATHIC REMEDY

Safety Sealed. Do not use if marked inner seal is disturbed or missing.

*CLAIMS BASED ON TRADITIONAL HOMEOPATHIC PRACTICE, NOT ACCEPTED
MEDICAL EVIDENCE. NOT FDA EVALUATED.

Distributed by Applied BioEnergetics LLC 205 W Russell Rd Las Vegas, NV 89148

res